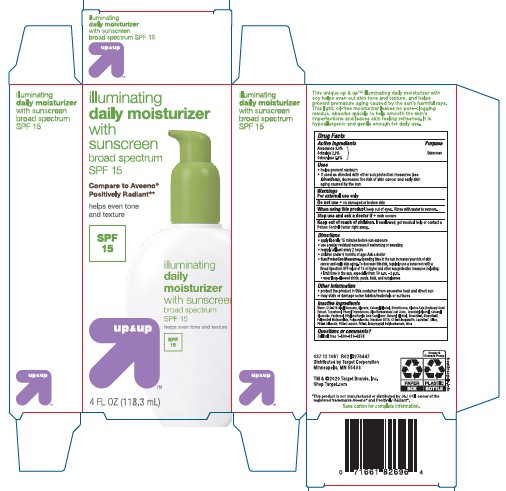 DRUG LABEL: Up and Up
NDC: 11673-934 | Form: LOTION
Manufacturer: TARGET CORPORATION
Category: otc | Type: HUMAN OTC DRUG LABEL
Date: 20241014

ACTIVE INGREDIENTS: OCTISALATE 20 mg/1 mL; OCTINOXATE 75 mg/1 mL; AVOBENZONE 30 mg/1 mL
INACTIVE INGREDIENTS: TITANIUM DIOXIDE; GLYCOL DILAURATE; PEG-4 LAURATE; BENZYL ALCOHOL; C13-14 ISOPARAFFIN; ACRYLIC ACID/ETHYLENE COPOLYMER (600 MPA.S); POLYACRYLAMIDE (1500 MW); ARACHIDYL GLUCOSIDE; DIMETHICONE; BENZALKONIUM CHLORIDE; SOYBEAN OIL; PANTHENOL; SODIUM HYDROXIDE; STEARETH-21; CETOSTEARYL ALCOHOL; ARACHIDYL ALCOHOL; PHENYL TRIMETHICONE; SILICON DIOXIDE; POLY(METHYL METHACRYLATE; 450000 MW); POLYETHYLENE GLYCOL 200; GLYCERIN; EDETATE DISODIUM; ANHYDROUS CITRIC ACID; ALKYL (C12-15) BENZOATE; WATER; BUTYLATED HYDROXYTOLUENE; CETEARYL GLUCOSIDE; DOCOSANOL; MICA; LAURETH-7; PHENOXYETHANOL; IODOPROPYNYL BUTYLCARBAMATE; STEARETH-2; ALCOHOL

Up and Up Illuminating Daily Moisturizer with Sunscreen Broad Spectrum SPF 15

Active ingredients

Avobenzone 3.0%, Octinoxate 7.5%, Octisalate 2.0%

Purpose

Sunscreen

Uses

- helps prevent sunburn
- if used as directed with other sun protection measures (see Directions), decreases the risk of skin cancer and early aging caused by the sun

Warnings

For external use only

Do not use

• on damaged or broken skin.

When using this product

• keep out of eyes. Rinse with water to remove.

Stop use and ask a doctor if

• rash occurs.

Keep out of reach of children.

If swallowed, get medical help or contact a Poison Control Center right away.

Directions

- apply liberally 15 minutes before sun exposure.
- reapply:
- after 80 minutes of swimming or sweating
- immediately after towel drying
- at least every 2 hours
- children under 6 months of age: Ask a doctor
- Sun Protection Measures. Spending time in the sun increases your risk of skin cancer and early skin aging. To decrease this risk, regularly use a sunscreen with a Broad Spectrum SPF value of 15 or higher and other sun protection measures including:
- limit time in the sun especially from 10 a.m. – 2 p.m.
- wear long-sleeved shirts, pants, hats, and sunglasses

Other information

- protect the product in this container from excessive heat and direct sun
- may stain or damage some fabrics, materials or surfaces

Inactive ingredients

Water, C12-15 Alkyl Benzoate, Glycerin, Cetearyl Alcohol, Dimethicone, Glycine Soja (Soybean) Seed Extract, Phenyl Trimethcione, Arachidyl Alcohol, Cetearyl Glucoside, Phenoxyethanol, Benzyl Alcohol, Panthenol, Ethylene/ Acrylic Acid Copolymer, Behenyl Alcohol, Steareth-2, Fragrance, Steareth-21, Polymethyl Methacrylate, Polyacrylamide, Arachidyl Glucoside, Disodium EDTA, C13-14 Isoparaffin, Laureth-7, Silica, Benzalkonium Chloride, Iodopropynyl Butylcarbamate, PEG-4 Dilaurate, PEG-4 Laurate, PEG-4, Alcohol, BHT, Sodium Hydroxide, Citric Acid, Titanium Dioxide, Mica

PACKAGE LABEL

Up and Up Illuminating Daily Moisturizer with Sunscreen Broad Spectrum SPF 15

4 FL OZ (118.3 mL)

NDC 11673-934-04 Bottle

NDC 11673-934-05 Carton